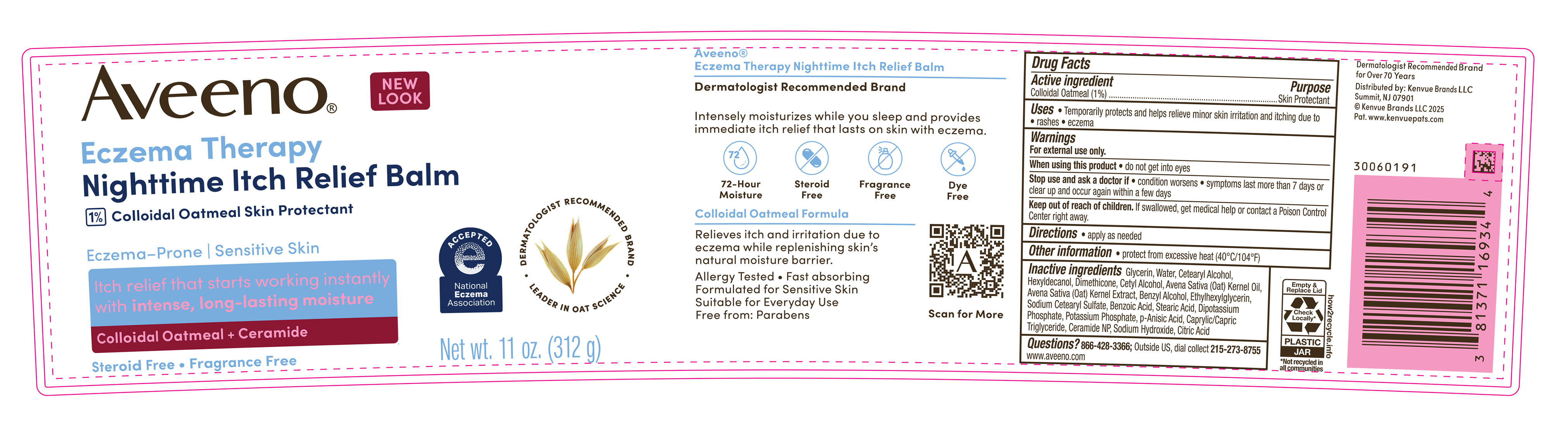 DRUG LABEL: Aveeno Eczema Therapy Nighttime Itch Relief Balm
NDC: 69968-0772 | Form: CREAM
Manufacturer: Kenvue Brands LLC
Category: otc | Type: HUMAN OTC DRUG LABEL
Date: 20260204

ACTIVE INGREDIENTS: OATMEAL 10 mg/1 g
INACTIVE INGREDIENTS: GLYCERIN; WATER; CETOSTEARYL ALCOHOL; HEXYLDECANOL; BENZYL ALCOHOL; SODIUM CETOSTEARYL SULFATE; BENZOIC ACID; DIBASIC POTASSIUM PHOSPHATE; POTASSIUM PHOSPHATE, UNSPECIFIED FORM; P-ANISIC ACID; SODIUM HYDROXIDE; DIMETHICONE; CETYL ALCOHOL; STEARIC ACID; OAT; CITRIC ACID MONOHYDRATE; ETHYLHEXYLGLYCERIN; CERAMIDE NP; MEDIUM-CHAIN TRIGLYCERIDES; OAT KERNEL OIL

Aveeno Eczema Therapy Nighttime Itch Relief Balm

Drug Facts

Active Ingredient

Colloidal Oatmeal 1%

Purpose

Skin Protectant

Uses

Temporarily protects and helps relieve minor skin irritation and itching due to

- • rashes
- • eczema

Warnings

For external use only.

When using this product

- do not get into eyes

Stop use and ask a doctor if

- condition worsens
- symptoms last more than 7 days or clear up and occur again within a few days

Keep out of reach of children. If swallowed, get medical help or contact a Poison Control Center right away.

Directions

- apply as needed

Other Information

- protect from excessive heat (40°C/104°F)

Inactive Ingredients

Glycerin, Water, Cetearyl Alcohol, Hexyldecanol, Dimethicone, Cetyl Alcohol, Avena Sativa (Oat) Kernel Oil, Avena Sativa (Oat) Kernel Extract, Benzyl Alcohol, Ethylhexylglycerin, Sodium Cetearyl Sulfate, Benzoic Acid, Stearic Acid, Dipotassium Phosphate, Potassium Phosphate, p-Anisic Acid, Caprylic/Capric Triglyceride, Ceramide NP, Sodium Hydroxide, Citric Acid

Questions?

866-428-3366; Outside US, dial collect 215-273-8755

www.aveeno.com

Distributed by:

Kenvue Brands LLC
Summit, NJ 07901

PRINCIPAL DISPLAY PANEL - 312 g Jar

NEW LOOK

Aveeno®

Eczema Therapy

Nighttime Itch Relief Balm

1% Colloidal Oatmeal Skin Protectant

Eczema-Prone | Sensitive Skin

Itch relief that starts working instantly

with intense, long-lasting moisture

Colloidal Oatmeal + Ceramide

Steroid Free • Fragrance Free

ACCEPTED

e

National

Eczema

Association

DERMATOLOGIST RECOMMENDED BRAND

LEADER IN OAT SCIENCE

Net wt. 11 oz. (312 g)